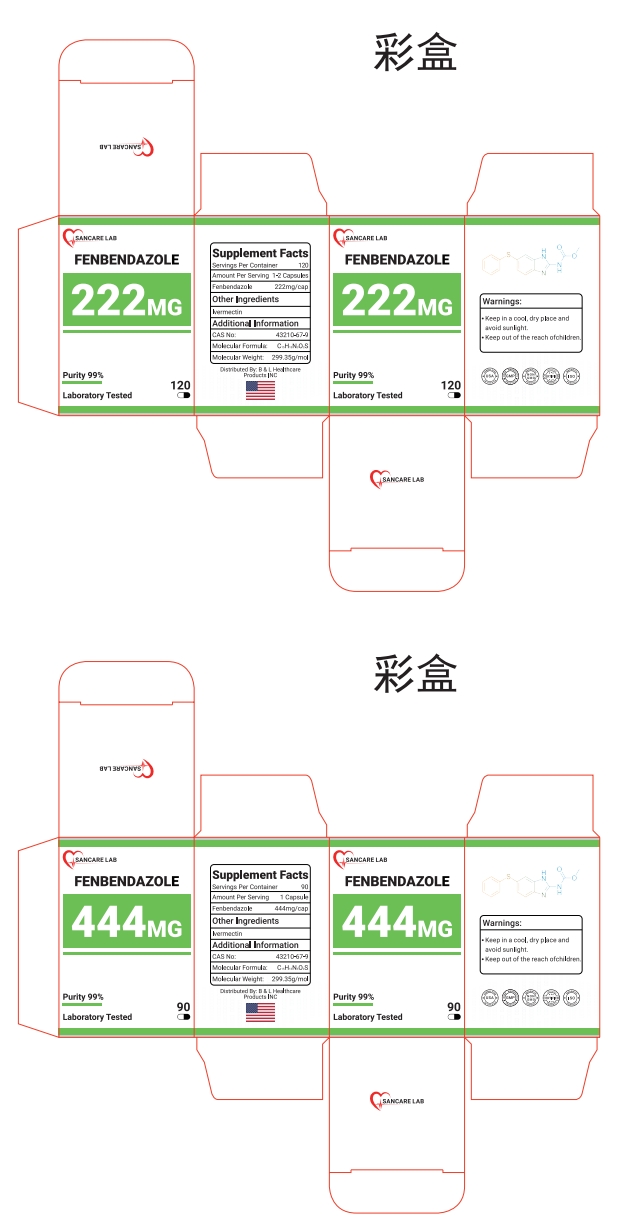 DRUG LABEL: Fenbendazole 222 MG
NDC: 85130-100 | Form: CAPSULE
Manufacturer: B & L Healthcare Products INC
Category: otc | Type: HUMAN OTC DRUG LABEL
Date: 20250423

ACTIVE INGREDIENTS: FENBENDAZOLE 299.35 mg/1 mol
INACTIVE INGREDIENTS: IVERMECTIN 12 mg/1 mol

ACTIVE INGREDIENT

Febendazole

INACTIVE INGREDIENT

Ivermectin

Keep out of the reach of children.

OTHER SAFETY INFORMATION

Keep in a cool, dry place and avoid sunlight.

DOSAGE AND ADMINISTRATION

2 capsules per day

PURPOSE

Dewormer

WARNINGS

These statements have not been evaluated by the Food and DrugAdministration.

This product is not intended to diagnose, treat, cure, or prevent any diseases.

INDICATIONS AND USAGE

Dewormer